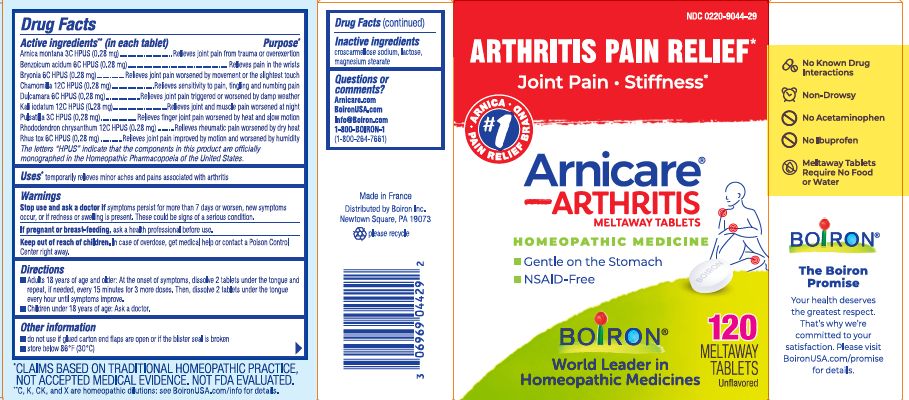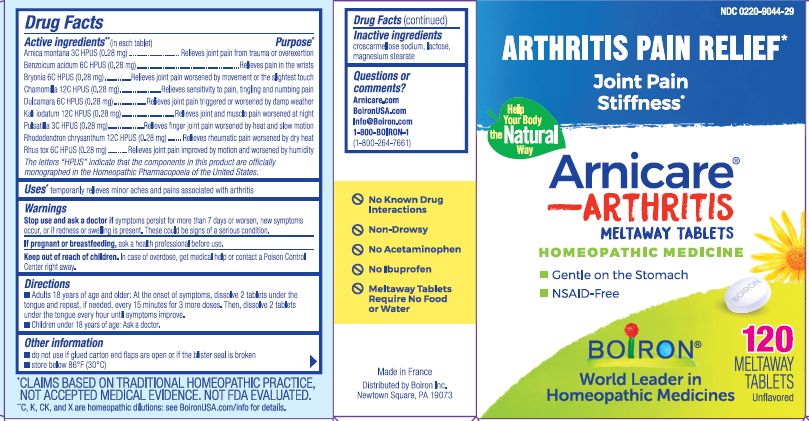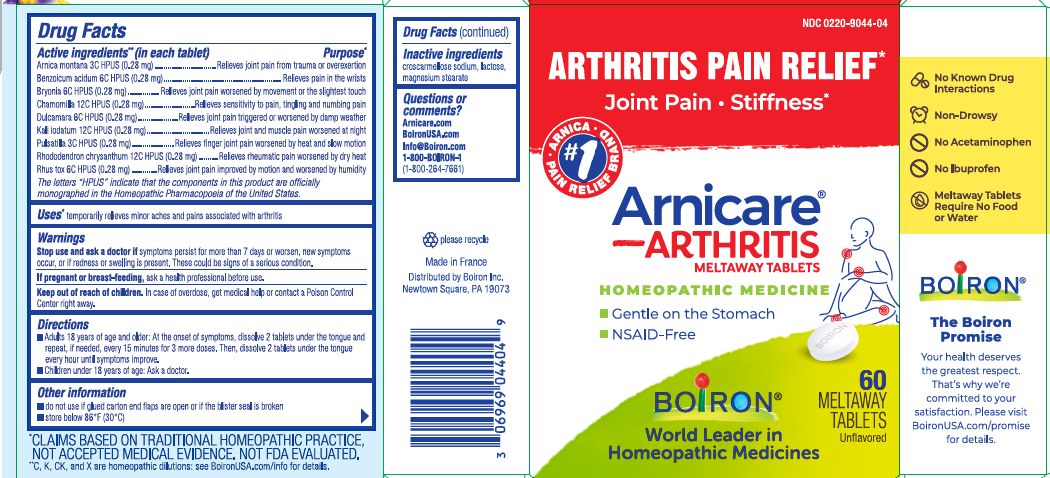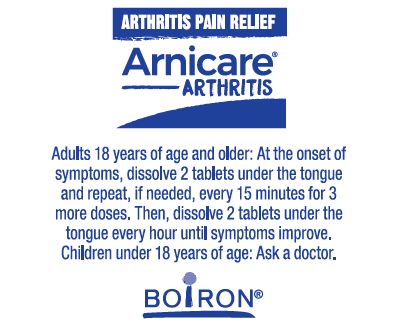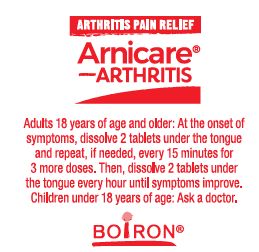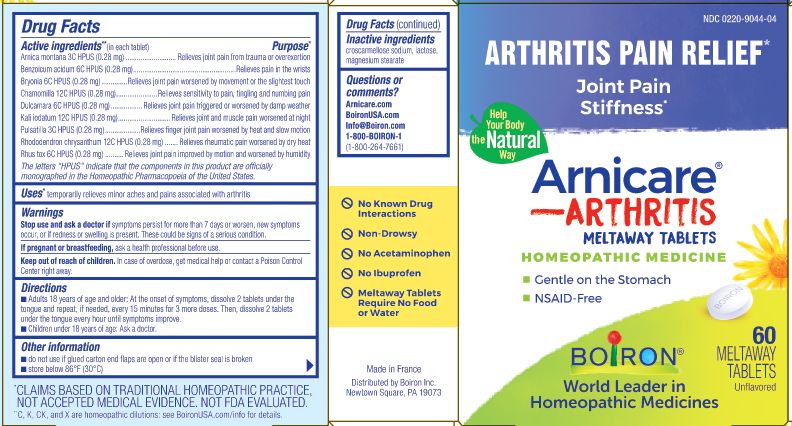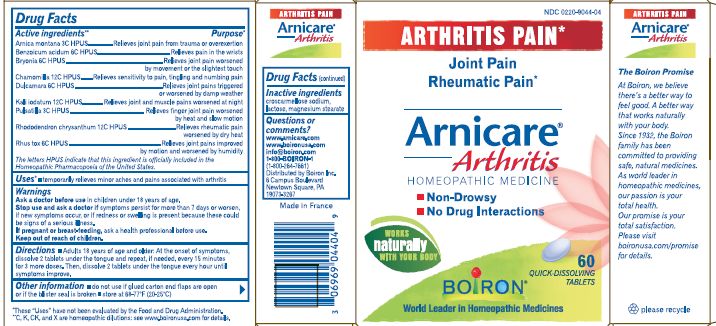 DRUG LABEL: Arnicare Arthritis
NDC: 0220-9044 | Form: TABLET
Manufacturer: Laboratoires Boiron
Category: homeopathic | Type: HUMAN OTC DRUG LABEL
Date: 20250316

ACTIVE INGREDIENTS: ARNICA MONTANA 3 [hp_C]/1 1; BENZOIC ACID 6 [hp_C]/1 1; BRYONIA ALBA ROOT 6 [hp_C]/1 1; MATRICARIA RECUTITA 12 [hp_C]/1 1; SOLANUM DULCAMARA TOP 6 [hp_C]/1 1; POTASSIUM IODIDE 12 [hp_C]/1 1; PULSATILLA VULGARIS 3 [hp_C]/1 1; RHODODENDRON AUREUM LEAF 12 [hp_C]/1 1; TOXICODENDRON PUBESCENS LEAF 6 [hp_C]/1 1
INACTIVE INGREDIENTS: CROSCARMELLOSE SODIUM; LACTOSE; MAGNESIUM STEARATE

Arnicare Arthritis

Active ingredients** (in each tablet)

Arnica Montana 3C HPUS (0.28 mg)

Benzoicum acidum 6C HPUS (0.28 mg)

Bryonia alba 6C HPUS (0.28 mg)

Chamomilla 12C HPUS (0.28 mg)

Dulcamara 6C HPUS (0.28 mg)

Kali iodatum 12C HPUS (0.28 mg)

Pulsatilla 3C HPUS (0.28 mg)

Rhododendron chrysanthum 12C HPUS (0.28 mg)

Rhus tox 6C HPUS (0.28 mg)

The letters "HPUS" indicate that the components in this product are officially monographed in the Homeopathic Pharmacopoeia of the United States.

Purpose*

Arnica Montana 3C HPUS (0.28 mg) ...Relieves joint pain from trauma or overexertion
Benzoicum acidum 6C HPUS (0.28 mg) ...Relieves pain in the wrists
Bryonia alba 6C HPUS (0.28 mg) ...Relieves joint pain worsened by movement or the slightest touch
Chamomilla 12C HPUS (0.28 mg) ...Relieves sensitivity to pain, tingling and numbing pain
Dulcamara 6C HPUS (0.28 mg) ...Relieves joint pain triggered or worsened by damp weather
Kali iodatum 12C HPUS (0.28 mg) ...Relieves joint and muscle pain worsened at night
Pulsatilla 3C HPUS (0.28 mg) ...Relieves finger joint pain worsened by heat and slow motion
Rhododendron chrysanthum 12C HPUS (0.28 mg) ...Relieves rheumatic pain worsened by dry heat
Rhus toxicodendron 6C HPUS (0.28 mg) ...Relieves joint pain improved by motion and worsened by humidity

Uses*

Temporary relieves minor aches and pains associated with arthritis

Stop use and ask a doctor if symptoms persist for more than 7 days or worsen, new symptoms occur, or if redness or swelling is present. These could be signs of a serious condition.

PREGNANCY OR BREAST FEEDING

If pregnant or breast-feeding, ask a health professional before us.

Keep out of reach of children. In case of overdose, get medical help or contact a Poison Control Center right away.

Directions

Adults 18 years of age and older: At the onset of symptoms, dissolve 2 tablets under the tongue and repeat, if needed, every 15 minutes for 3 more doses. Then, dissolve 2 tablets under the tongue every hour until symptoms improve.

Children under 18 years of age: Ask a doctor.

INACTIVE INGREDIENT

croscarmellose sodium, lactose, magnesium stearate

do not use if glued carton end flaps are open or if the blister seal is broken

store below 86°F (30°C)

No Known Drug Interactions

Non-Drowsy

No Acetaminophen

No Ibuprofen

Meltaway Tablets Require No Food or Water

Arthritis Pain Relief*

Joint Pain Stiffness*

Gentle on the Stomach

NSAID-Free

60 Meltaway Tablets unflavored

120 Meltaway Tablets unflavored

*CLAIMS BASE ON TRADITIONAL HOMEOPATHIC PRACTICE, NOT ACCEPTED MEDICAL EVIDENCE. NOT FDA EVALUATED.

**C, K, CK, and X are homeopathic dilutions: see BoironUSA.com/info for details

Questions or Comments?
Arnicare.com

BoironUSA.com

Info@boiron.comm
1-800-BOIRON-1
(1-800-264-7661)
Made in France

Distributed by Boiron, Inc.

Newtown Square, PA 19073